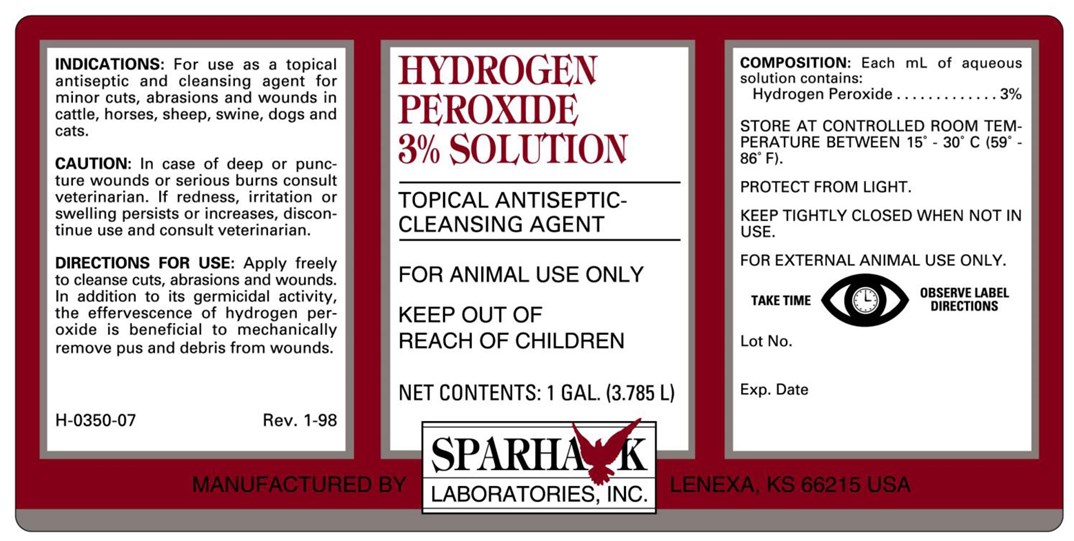 DRUG LABEL: HYDROGEN PEROXIDE
NDC: 58005-303 | Form: LIQUID
Manufacturer: Sparhawk Laboratories, Inc.
Category: animal | Type: OTC ANIMAL DRUG LABEL
Date: 20161103

ACTIVE INGREDIENTS: HYDROGEN PEROXIDE 0.03 mL/1 mL

HYDROGEN PEROXIDE 3% SOLUTION

INDICATIONS AND USAGE

TOPICAL ANTISEPTIC-CLEANING AGENT

FOR ANIMAL USE ONLY

KEEP OUT OF REACH OF CHILDREN

FOR EXTERNAL ANIMAL USE ONLY

INDICATIONS

For use as a topical antiseptic and cleaning agent for minor cuts, abrasions and wounds in cattle, horses, sheep, swine, dogs and cats.

CAUTION

In case of deep or puncture wounds or serious burns consult veterinarian. If redness, irritation or swelling persists or increases, discontinue use and consult veterinarian.

DIRECTIONS FOR USE

Apply freely to cleanse cuts, abrasions and wounds. In addition to its germicidal activity, the effervescence of hydrogen peroxide is beneficial to mechanically remove pus and debris from wounds.

COMPOSITION

Each mL of aqueous solution contains
Hydrogen Peroxide ................. 3%

STORAGE AND HANDLING

STORE AT CONTROLLED ROOM TEMPERATURE BETWEEN 15o - 30oC (59o-86oF).

PROTECT FROM LIGHT.

KEEP TIGHTLY CLOSED WHEN NOT IN USE.

TAKE TIME OBSERVE LABEL DIRECTIONS